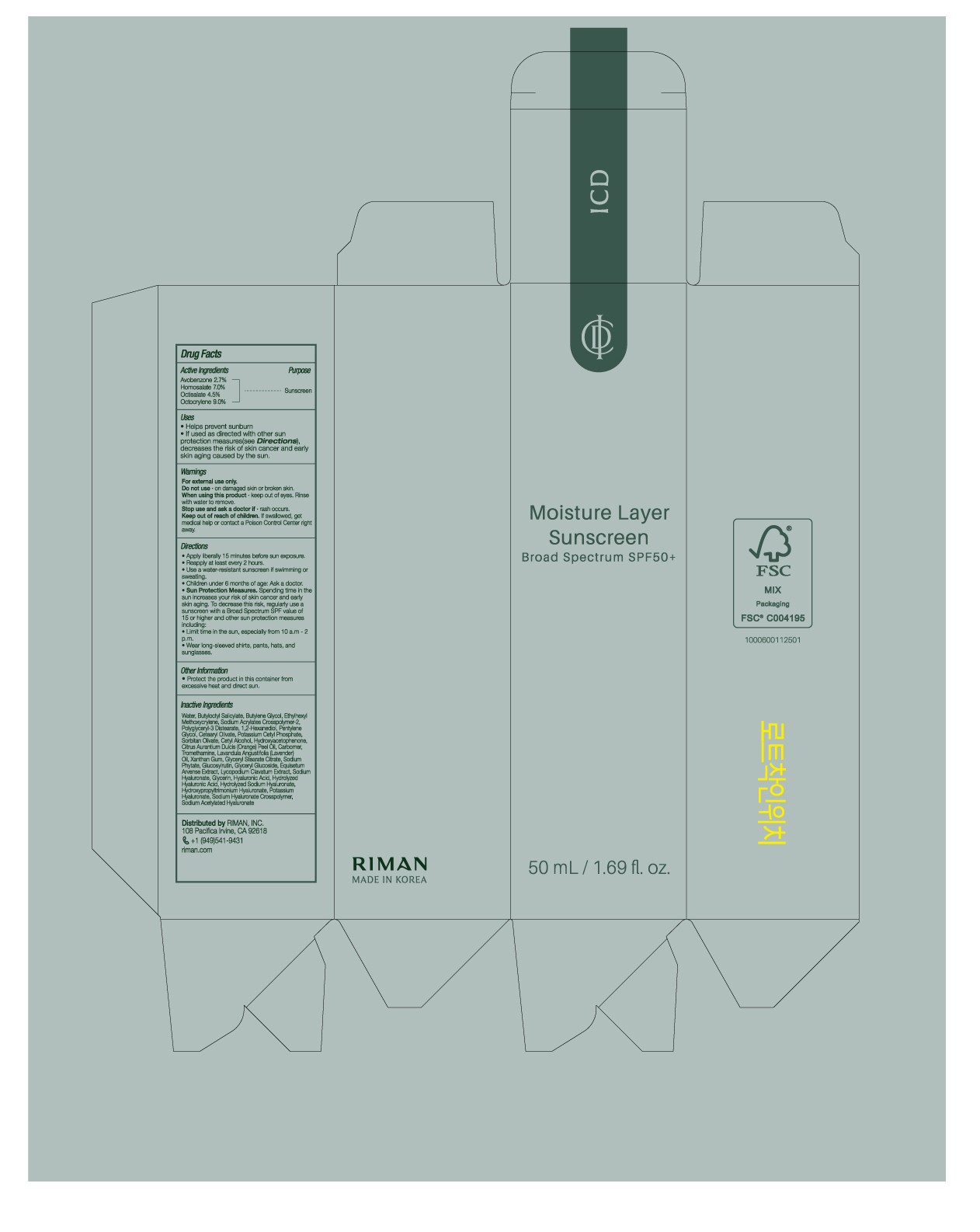 DRUG LABEL: ICD Moisture Layer Sunscreen
NDC: 85938-006 | Form: CREAM
Manufacturer: ICD Moisture Layer Sunscreen
Category: otc | Type: HUMAN OTC DRUG LABEL
Date: 20250718

ACTIVE INGREDIENTS: OCTOCRYLENE 9 g/100 mL; HOMOSALATE 7 g/100 mL; BUTYL METHOXYDIBENZOYLMETHANE 2.7 g/100 mL; ETHYLHEXYL SALICYLATE 4.5 g/100 mL
INACTIVE INGREDIENTS: XANTHAN GUM; HYDROXYACETOPHENONE; TROMETHAMINE; SODIUM ACETYLATED HYALURONATE; POTASSIUM CETYL PHOSPHATE; BUTYLOCTYL SALICYLATE; SODIUM ACRYLATES CROSSPOLYMER-2; PENTYLENE GLYCOL; CETYL ALCOHOL; CETEARYL OLIVATE; CARBOMER; LAVANDULA ANGUSTIFOLIA (LAVENDER) OIL; GLYCERYL GLUCOSIDE; HYALURONIC ACID; 1,2-HEXANEDIOL; SORBITAN OLIVATE; GLYCERYL STEARATE CITRATE; BUTYLENE GLYCOL; POLYGLYCERYL-3 DISTEARATE; CITRUS AURANTIUM DULCIS (ORANGE) PEEL OIL; SODIUM PHYTATE; GLYCERIN; WATER; ETHYLHEXYL METHOXYCRYLENE

Directions
• Apply liberally 15 minutes before sun exposure
• Reapply at least every 2 hours
• Use a water-resistant sunscreen if swimming or sweating
• Children under 6 months of age: Ask a doctor
• Sun Protection Measures. Spending time in the sun increases your risk of skin
cancer and early skin aging. To decrease this risk regularly use a sunscreen with
a Broad Spectrum SPF value of 15 or higher and other sun protection
measures including:
• Limit time in the sun, especially from 10 a.m.-2 p.m.
• Wear long-sleeved shirts, pants, hats, and sunglasses.

WARNINGS

For external use only.

Do not use on damaged or broken skin.

When using this product keep out of eyes. Rinse with water to remove.

Stop use and ask a doctor if rash occurs.

Keep out of reach of children. If product is swallowed, get medical help or contact a Poison Control Center right away.

INACTIVE INGREDIENT

Water, Butyloctyl Salicylate, Butylene Glycol, Ethylhexyl Methoxycrylene, Sodium Acrylates Crosspolymer-2, Polyglyceryl-3 Distearate, 1,2-Hexanediol, Pentylene Glycol, Cetearyl Olivate, Potassium Cetyl Phosphate, Sorbitan Olivate, Cetyl Alcohol, Hydroxyacetophenone, Citrus Aurantium Dulcis (Orange) Peel Oil, Carbomer, Tromethamine, Lavandula Angustifolia (Lavender) Oil, Xanthan Gum, Glyceryl Stearate Citrate, Sodium Phytate, Glucosylrutin, Glyceryl Glucoside, Equisetum Arvense Extract, Lycopodium Clavatum Extract, Sodium Hyaluronate, Glycerin, Hyaluronic Acid, Hydrolyzed Hyaluronic Acid, Hydrolyzed Sodium Hyaluronate, Hydroxypropyltrimonium Hyaluronate, Potassium Hyaluronate, Sodium Hyaluronate Crosspolymer, Sodium Acetylated Hyaluronate

Uses

• Helps prevent sunburn

• If used as directed with other sun protection measures (see Directions), decreases the risk of skin cancer and early skin aging caused by the sun.

Keep out of reach of children. if product is swallowed, get medical help or contact a Poison Control Center right away.

Purpose

Sunscreen

Other Information

• Protect the product in this container from excessive heat and direct sun.